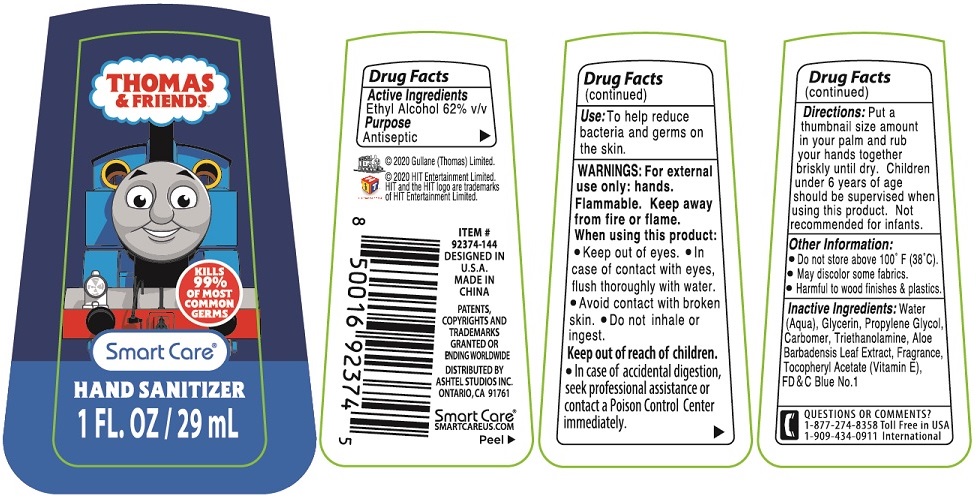 DRUG LABEL: Thomas and Friends Hand Sanitizer
NDC: 72285-010 | Form: GEL
Manufacturer: Yozzi Co.,ltd
Category: otc | Type: HUMAN OTC DRUG LABEL
Date: 20200630

ACTIVE INGREDIENTS: ALCOHOL 62 mL/100 mL
INACTIVE INGREDIENTS: WATER; GLYCERIN; PROPYLENE GLYCOL; CARBOMER HOMOPOLYMER, UNSPECIFIED TYPE; TROLAMINE; ALOE VERA LEAF; .ALPHA.-TOCOPHEROL ACETATE; FD&C BLUE NO. 1

THOMAS & FRIENDS HAND SANITIZER

Active Ingredients

Ethyl Alcohol 62% v/v

Purpose

Antiseptic

Use:

To help reduce bacteria and germs on the skin.

WARNINGS:

For external use only: hands.

Flammable. Keep away from fire or flame.

When using this product:

• Keep out of eyes. • In case of contact with eyes, flush thoroughly with water.

• Avoid contact with broken skin. • Do not inhale or ingest.

Keep out of reach of children.

• In case of accidental ingestion, seek professional assistance or contact a Poison Control Center immediately.

Directions:

Put a thumbnail size amount in your palm and rub your hands together briskly until dry. Children under 6 years of age should be supervised when using this product. Not recommended for infants.

Other Information:

• Do not store above 100° F (38°C)

• May discolor some fabrics.

• Harmful to wood finishes & plastics.

Inactive Ingredients:

Water (Aqua), Glycerin, Propylene Glycol, Carbomer, Triethanolamine, Aloe Barbadensis Leaf Extract, Fragrance, Tocopheryl Acetate (Vitamin E), FD&C Blue No. 1

QUESTIONS OR COMMENTS?

1-877-274-8358 Toll Free in USA

1-909-434-0911 International

KILLS 99% OF MOST COMMON GERMS

Smart Care®

© 2020 Gullane (Thomas) Limited

© 2020 HIT Entertainment Limited.

HIT and the HIT logo are trademarks of HIT Entertainment Limited.

DESIGNED IN U.S.A.

MADE IN CHINA

PATENTS, COPYRIGHTS AND TRADEMARKS GRANTED OR PENDING WORLDWIDE

DISTRIBUTED BY

ASHTEL STUDIOS INC.

ONTARIO, CA 91761

SMARTCAREUS.COM